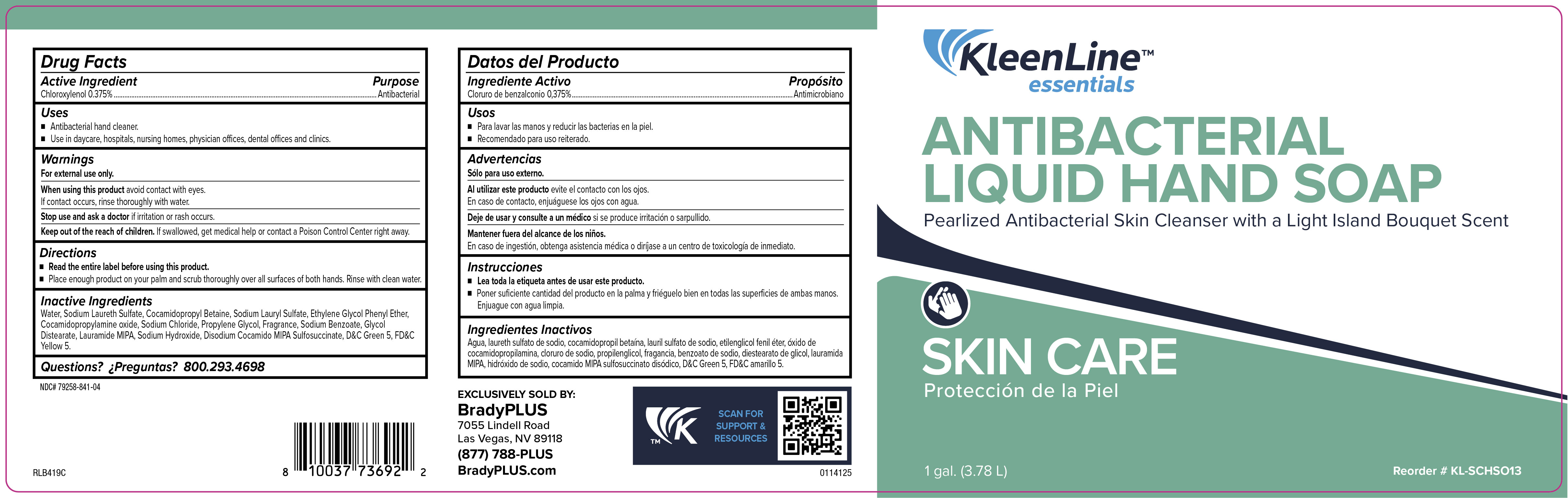 DRUG LABEL: KleenLine Essentials Antibacterial LotionSkin Cleanser
NDC: 79258-841 | Form: LIQUID
Manufacturer: Brady Industries
Category: otc | Type: HUMAN OTC DRUG LABEL
Date: 20241216

ACTIVE INGREDIENTS: CHLOROXYLENOL 4 mg/1 mL
INACTIVE INGREDIENTS: D&C GREEN NO. 5; SODIUM LAURYL SULFATE; COCAMIDOPROPYLAMINE OXIDE; SODIUM LAURETH SULFATE; 2-ISOBUTYL-4-METHYLTETRAHYDROPYRAN-4-OL; HEXYL SALICYLATE; LINALOOL; TRIBASIC CALCIUM PHOSPHATE; WATER; PHENYLETHYL ALCOHOL; VERDYL ACETATE; 2-TERT-BUTYLCYCLOHEXYL ACETATE; .GAMMA.-UNDECALACTONE; SODIUM CARBONATE; SODIUM HYDROXIDE; SODIUM CHLORIDE; PROPYLENE GLYCOL; PHENOXYETHANOL; SODIUM ALUMINIUM SILICATE; COCAMIDOPROPYL BETAINE; FD&C YELLOW NO. 5; HEXAHYDRO-4,7-METHANOINDEN-6-YL PROPIONATE; .ALPHA.-HEXYLCINNAMALDEHYDE; LAURIC ISOPROPANOLAMIDE; BENZYL SALICYLATE; ETHYLENE OXIDE; .ALPHA.-AMYLCINNAMALDEHYDE; BENZYL ACETATE; 2,6-DIMETHYL-5-HEPTENAL; CALCIUM SILICATE; 1-(2,3,8,8-TETRAMETHYL-1,2,3,4,5,6,7,8-OCTAHYDRONAPHTHALEN-2-YL)ETHANONE; 3-(3,4-METHYLENEDIOXYPHENYL)-2-METHYLPROPANAL; GLYCOL DISTEARATE; ETHYLENE BRASSYLATE; .BETA.-CITRONELLOL, (+/-)-; 4-ACETOXY-3-PENTYLTETRAHYDROPYRAN; DIHYDROMYRCENOL; SODIUM BENZOATE

Kleenline Essentials Antibacterial Lotionskin Cleanser

active ingredient

Chloroxylenol 0.4%

KEEP OUT OF REACH OF CHILDREN

Keep out of reach of childtren. If swallowed, get medical help or contact poison control section right away

PURPOSE

Antibacterial

INACTIVE INGREDIENT

Water, Sodium Laureth Sulfate, Cocamidopropyl Betaine, Sodium Lauryl Sulfate, Ethylene Glycol Phenyl Ether, Cocamidopropyl Amine Oxide, Sodiun Chloride, Propylene Glycol, Sodium Benzoate, Glycol Distearate, Fragance, Lauramide MIPA, Sodium Hydroxide, Disodium Cocamido MIPA Sulfosuccinate, D&C Green 5, FD&C Yellow 5, Methylchlorosithiazolinone, Methylisothiazolinone

INSTRUCTIONS FOR USE

Read entire label before using this product

Place enough product on your pam and scrub thoroughly over all surfaces of both hands. Risne with clean water.

USER SAFETY WARNINGS

For external use only

when using this product avoid contact with eyes

If contact occurs rinse thoroughly wiht water

Stop use adn ask doctor if irriitation or rash occurs

INDICATIONS AND USAGE

Anticacteial hand cleaner

use in daycare, hospitals, nursing homes, physicians offices, dental offices and clinics

DOSAGE AND ADMINISTRATION

Place enough product on your palmand scrub thoroughly over all surfaces of both hands. Rinse with clean water

warnings

For external use only

When using this product avoid contact with eyes

If contact occurs, rinse thoroughly with water

Stop use and ask doctor if irritation or rash occurs

WARNINGS

For external use only

When using this product avoid contact with eyes

If contact occurs, rinse thoroughly with water

Stop use and ask doctor if irritation or rash occurs